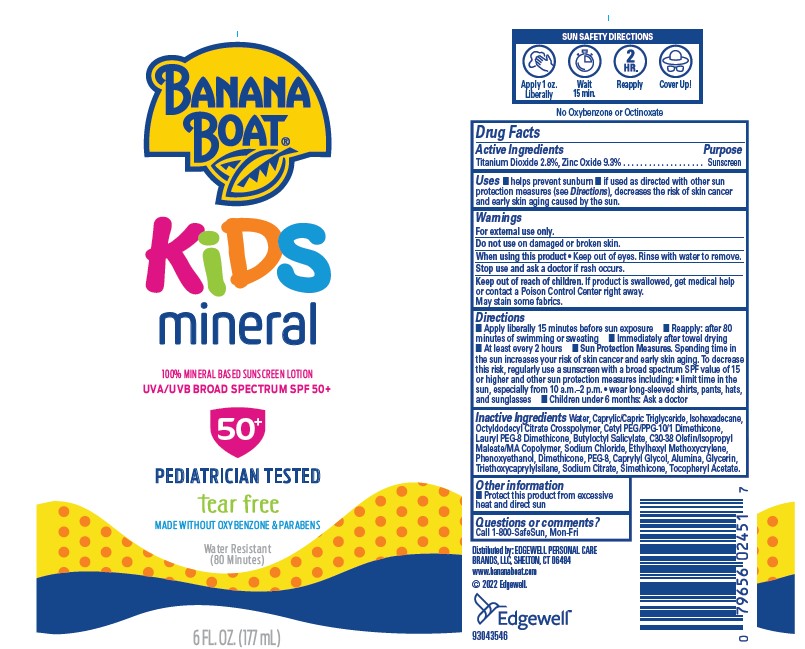 DRUG LABEL: BANANA BOAT
NDC: 63354-874 | Form: LOTION
Manufacturer: Edgewell Personal Care Brands LLC
Category: otc | Type: HUMAN OTC DRUG LABEL
Date: 20250106

ACTIVE INGREDIENTS: TITANIUM DIOXIDE 3.5 g/100 g; ZINC OXIDE 9.3 g/100 g
INACTIVE INGREDIENTS: PEG-8; GLYCERIN; CAPRYLIC/CAPRIC TRIGLYCERIDE; SODIUM CITRATE; CETYL PEG/PPG-10/1 DIMETHICONE (HLB 2); LAURYL PEG-8 DIMETHICONE (300 CPS); CAPRYLYL GLYCOL; ALUMINA; BUTYLOCTYL SALICYLATE; DIMETHICONE; ISOHEXADECANE; SODIUM CHLORIDE; TRIETHOXYCAPRYLYLSILANE; WATER; ETHYLHEXYL METHOXYCRYLENE; PHENOXYETHANOL; .ALPHA.-TOCOPHEROL ACETATE

Active Ingredients

Titanium Dioxide 2.8%, Zinc Oxide 9.3%

Purpose

Sunscreen

Uses

• helps prevent sunburn • if used as directed with other sun protection measures (see Directions), decreases the risk of skin cancer
and early skin aging caused by the sun.

Warnings

For external use only.
May stain some fabrics.

Do not use

on damaged or broken skin.

When using this product

• Keep out of eyes. Rinse with water to remove.

Stop use and ask a doctor

if rash occurs.

Keep out of reach of children.

If product is swallowed, get medical help or contact a Poison Control Center right away.

Directions

• Shake well • Apply liberally 15 minutes before sun exposure • Reapply: after 80 minutes of swimming or sweating • Immediately after towel drying • At least every 2 hours • Sun Protection Measures. Spending time in the sun increases your risk of skin cancer and early skin aging. To decrease this risk, regularly use a sunscreen with a broad spectrum SPF value of 15 or higher and other sun protection measures including: • limit time in the sun, especially from 10 a.m.–2 p.m. • wear long-sleeved shirts, pants, hats, and sunglasses • Children under 6 months: Ask a doctor

Inactive Ingredients

Water, Caprylic/Capric Triglyceride, Isohexadecane, Octyldodecyl Citrate Crosspolymer, Cetyl PEG/PPG-10/1 Dimethicone, Lauryl PEG-8 Dimethicone, Butyloctyl Salicylate, C30-38 Olefin/Isopropyl Maleate/MA Copolymer, Sodium Chloride, Ethylhexyl Methoxycrylene, Phenoxyethanol, Dimethicone, PEG-8, Caprylyl Glycol, Alumina, Glycerin, Triethoxycaprylylsilane, Sodium Citrate, Simethicone, Tocopheryl Acetate.

Other information

• Protect this product from excessive heat and direct sun

Questions or comments?

Call 1-800-SafeSun, Mon-Fri

Principal Display Panel

BANANA BOAT

KIDS

Mineral

100% MINERAL BASED SUNSCREEN LOTION

UVA/UVB BROAD SPECTRUM SPF 50+

50+

PEDIATRICIAN TESTED

tear free

MADE WITHOUT OXYBENZONE & PARABENS

Water Resistant

(80 Minutes)

6 FL. OZ. (177 mL)